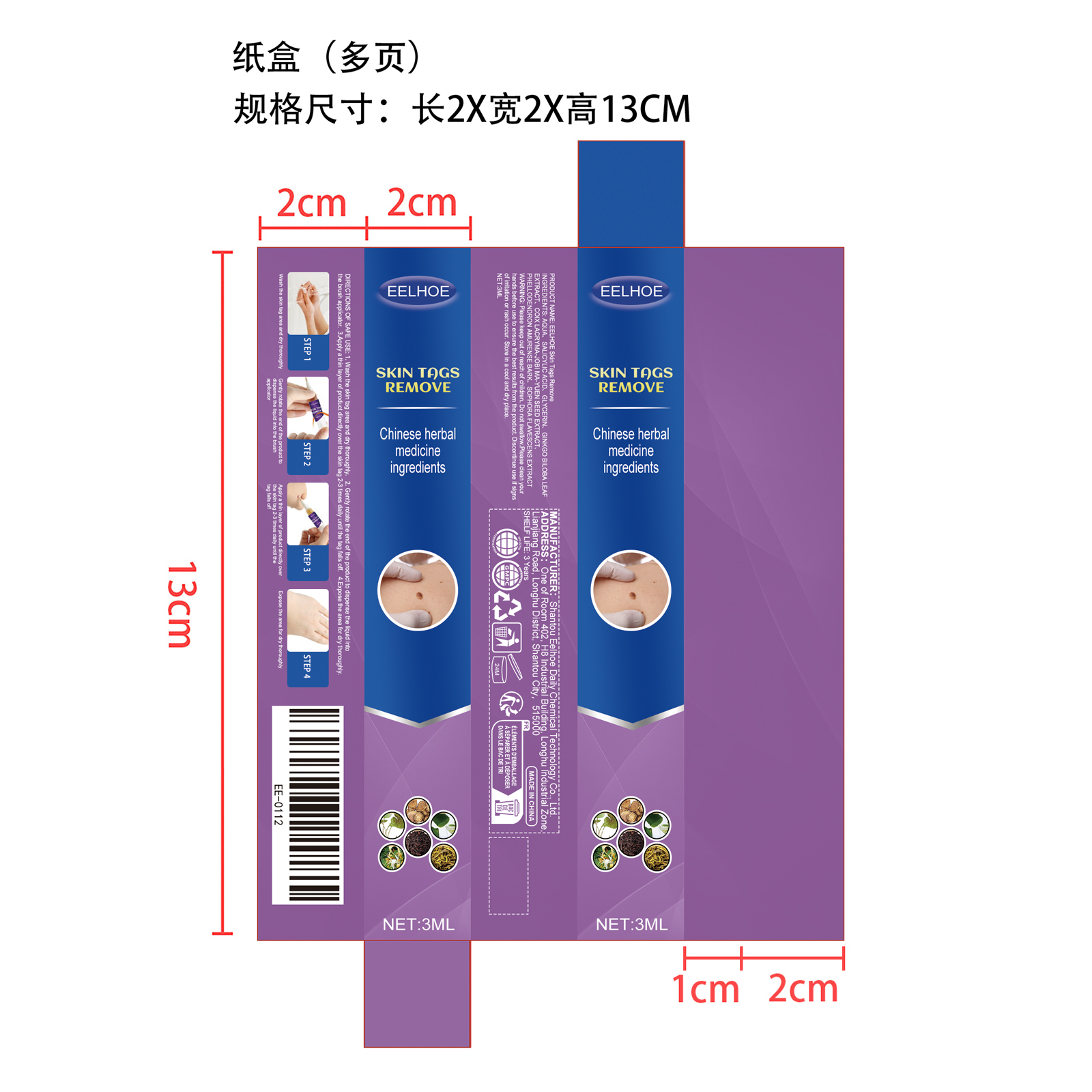 DRUG LABEL: EELHOE Skin Tags Remove
NDC: 85064-015 | Form: LIQUID
Manufacturer: Shantou Eelhoe Daily Chemical Technology Co., Ltd.
Category: otc | Type: HUMAN OTC DRUG LABEL
Date: 20251127

ACTIVE INGREDIENTS: GINKGO BILOBA LEAF 0.003 mg/3 mg; PHELLODENDRON AMURENSE BARK 0.003 mg/3 mg; COIX LACRYMA-JOBI MA-YUEN SEED 0.003 mg/3 mg; SOPHORA FLAVESCENS ROOT 0.003 mg/3 mg
INACTIVE INGREDIENTS: GLYCERIN 0.15 mg/3 mg; SALICYLIC ACID 0.24 mg/3 mg; AQUA 2.598 mg/3 mg

Active Ingeredient(s)

GINKGO BILOBA LEAF EXTRACT、COIX LACRYMA、JOBI MA-YUEN SEED EXTRACT、PHELLODENDRON AMURENSE BARK、SOPHORA FLAVESCENS EXTRACT

Purpose

1. Help the skin reduce the influence of foreign objects, gently remove warts on the skin, reduce the appearance of warts, and make the skin smoother.

2. The texture is light and non-sticky, the ingredients are mild, and it protects the skin around warts from being affected by warts.

3. Suitable for all types of skin, suitable for removing moles, spots, skin tags, etc.

Use

1. Wash the skin tag area and dry thoroughly.

2. Gently rotate the end of the product to dispense the liquid into the brush applicator.

3 Apply a thin layer of product directly over the skin tag 2-3 times daily until the tag falls off.

4.Expose the area for dry thoroughly.

Warnings

Please keep out of reach of children. Do not swallow.Please clean your hands before use to ensure the best results from the product. Discontinue use if signs of irritation or rash occur. Store in a cool and dry place.

Do not use

Discontinue use if signs of irritation or rash occur.

Stop Use

Discontinue use if signs of irritation or rash occur.

KEEP OUT OF REACH OF CHILDREN

Please keep out of reach of children. Do not swallow.

STORAGE AND HANDLING

Store in a cool and dry place.

INACTIVE INGREDIENT

AQUA、SALICYLIC ACID、GLYCERIN

INDICATIONS AND USAGE

1. Wash the skin tag area and dry thoroughly.

2. Gently rotate the end of the product to dispense the liquid into the brush applicator.

3 Apply a thin layer of product directly over the skin tag 2-3 times daily until the tag falls off.

4.Expose the area for dry thoroughly.

DOSAGE AND ADMINISTRATION

1. Wash the skin tag area and dry thoroughly.

2. Gently rotate the end of the product to dispense the liquid into the brush applicator.

3 Apply a thin layer of product directly over the skin tag 2-3 times daily until the tag falls off.

4.Expose the area for dry thoroughly.